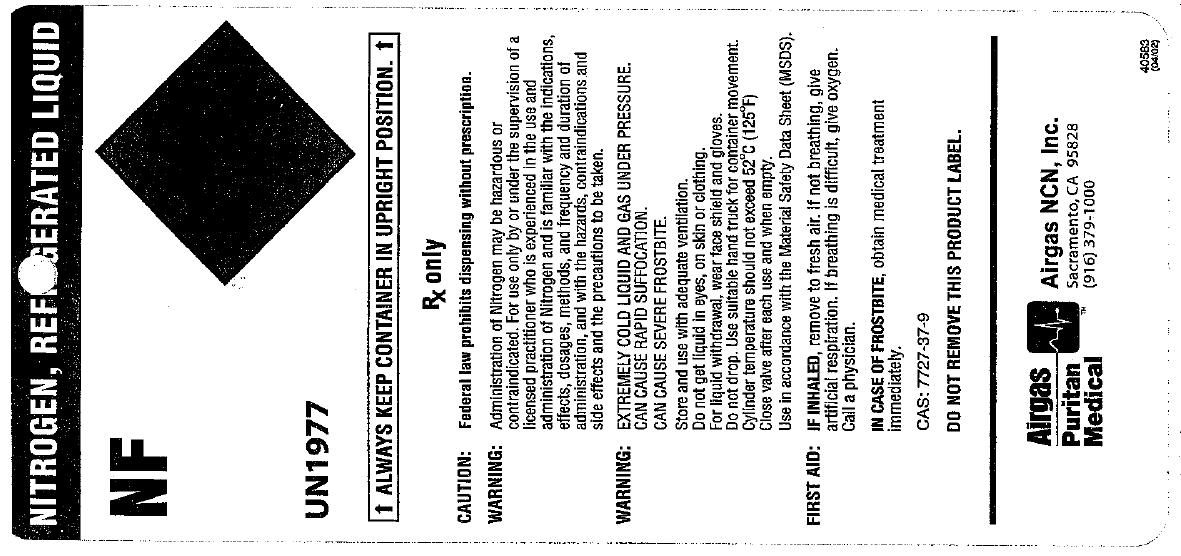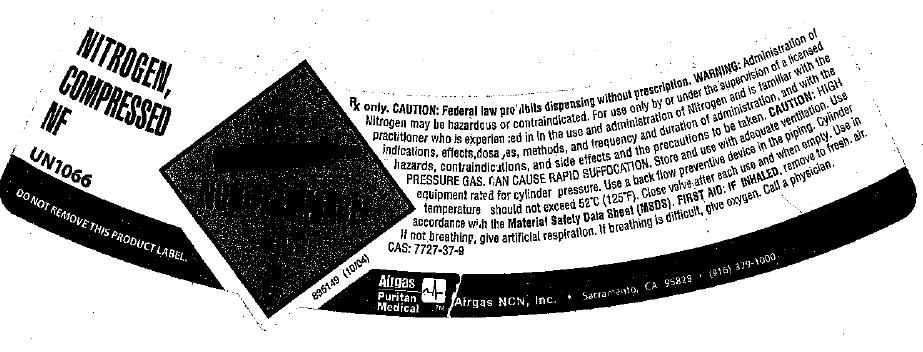 DRUG LABEL: Nitrogen
NDC: 58789-002 | Form: GAS
Manufacturer: Airgas Northern California and Nevada, Inc.
Category: prescription | Type: HUMAN PRESCRIPTION DRUG LABEL
Date: 20100430

ACTIVE INGREDIENTS: Nitrogen 992 mL/1 L

nitrogen

PACKAGE LABEL

NITROGEN, REFRIGERATED LIQUID
NF UN1977
ALWAYS KEEP CONTAINER IN UPRIGHT POSITION
Rx Only
CAUTION: Federal law prohibits dispensing without prescription.
WARNING: Administration of Nitrogen may be hazardous or contraindicated. For use only by or under the supervision of a licensed practitioner who is experienced in the use and administration of Nitrogen and is familiar with the indications, effects, dosages, methods, and frequency and duration of administration, and with the hazards, contraindications and side effects and the precautions to be taken.
WARNING: EXTREMELY COLD LIQUID AND GAS UNDER PRESSURE CAN CAUSE RAPID SUFFOCATION. CAN CAUSE SEVERE FROSTBITE. Store and use with adequate ventilation. Do not get liquid in eyes, on skin and clothing. For liquid withdrawal, wear face shield and gloves. Do not drop. Use suitable hand truck for container movement. Cylinder temperature should not exceed 52C(125F). Close valve after each use and when empty. Use in accordance with the Material Safety Data Sheets (MSDS).
FIRST AID: IF INHALED, remove to fresh air. If not breathing, give artificial respiration. If breathing is difficult, give oxygen. Call a physician.
IN CASE OF FROSTBITE, obtain medical treatment immediately.
CAS: 7727-37-9
AIRGAS PURITAN MEDICAL Airgas NCN, Inc. Sacramento, CA 95828 (916) 379-1000

PACKAGE LABEL

NITROGEN, COMPRESSED NF UN 1066
DO NOT REMOVE THIS PRODUCT LABEL
Rx Only. CAUTION: Federal law prohibits dispensing without prescription. WARNING: Administration of Nitrogen may be hazardous or contraindicated. For use only by or under the supervision of a licensed practitioner who is experienced in, In the use and administration of Nitrogen and is familiar with the indications , effects, dosages, methods and frequency and duration of administration, and with the hazards, contraindications, and side effects and the precautions to be taken. CAUTION: HIGH PRESSURE GAS. CAN CAUSE RAPID SUFFOCATION. Store and use with adequate ventilation. Use equipment rated for cylinder pressure. Use a back flow preventive device in the piping. Cylinder temperature should not exceed 52C (125F). Close valve after each use and when empty. Use in accordance with Material Safety Data Sheets (MSDS). FIRST AID: IF INHALED, remove to fresh air. If not breathing, give artificial respiration. If breathing is difficult, give oxygen. Call a physician. CAS 7727-37-9
835149 (10/04)
Airgas Medical Airgas NCN, Inc. Sacramento, CA 95828 (916) 379 1000